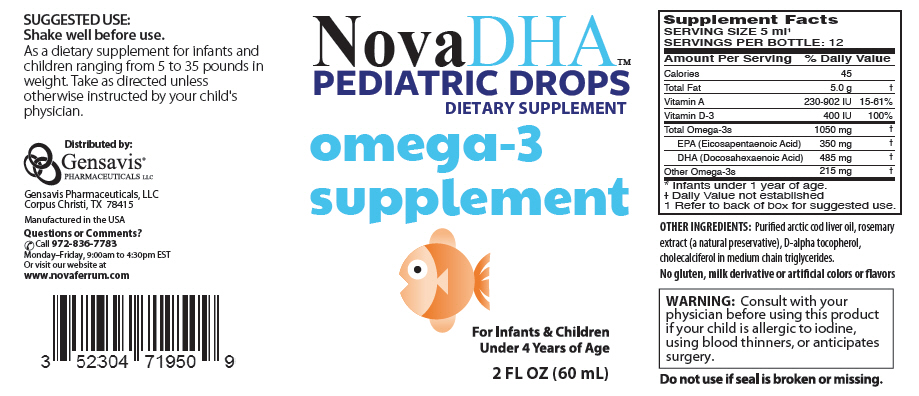 DRUG LABEL: NovaDHA 
NDC: 52304-719 | Form: LIQUID
Manufacturer: Gensavis Pharmaceuticals, LLC
Category: other | Type: DIETARY SUPPLEMENT
Date: 20160201

ACTIVE INGREDIENTS: Omega-3 Fatty Acids 1050 mg/5 mL; Cholecalciferol 400 [iU]/5 mL; .Alpha.-Tocopherol 6 mg/5 mL
INACTIVE INGREDIENTS: Rosemary

NovaDHA™
PEDIATRIC DROPS
DIETARY SUPPLEMENT

STATEMENT OF IDENTITY

Supplement Facts
SERVING SIZE 5 ml [Refer to back of box for suggested use.]
SERVINGS PER BOTTLE: 12
Amount Per Serving | % Daily Value
Calories | 45
Total Fat | 5.0 g | [Daily Value not established]
Vitamin A | 230-902 IU | 15-61%
Vitamin D-3 | 400 IU | 100%
Total Omega-3s | 1050 mg
EPA (Eicosapentaenoic Acid) | 350 mg
DHA (Docosahexaenoic Acid) | 485 mg
Other Omega-3s | 215 mg
* Infants under 1 year of age.

OTHER INGREDIENTS: Purified arctic cod liver oil, rosemary extract (a natural preservative), D-alpha tocopherol, cholecalciferol in medium chain triglycerides.

No gluten, milk derivative or artificial colors or flavors

WARNING

Consult with your physician before using this product if your child is allergic to iodine, using blood thinners, or anticipates surgery.

Do not use if seal is broken or missing.

SUGGESTED USE

Shake well before use.

As a dietary supplement for infants and children ranging from 5 to 35 pounds in weight. Take as directed unless otherwise instructed by your child's physician.

HEALTH CLAIM

Distributed by:
Gensavis®
PHARMACEUTICALS LLC

Gensavis Pharmaceuticals, LLC
Corpus Christi, TX 78415

Manufactured in the USA

Questions or Comments?
Call 972-836-7783
Monday–Friday, 9:00am to 4:30pm EST
Or visit our website at
www.novaferrum.com

PRINCIPAL DISPLAY PANEL - 60 mL Bottle Label

NovaDHA™
PEDIATRIC DROPS
DIETARY SUPPLEMENT

omega-3
supplement

For Infants & Children
Under 4 Years of Age

2 FL OZ (60 mL)